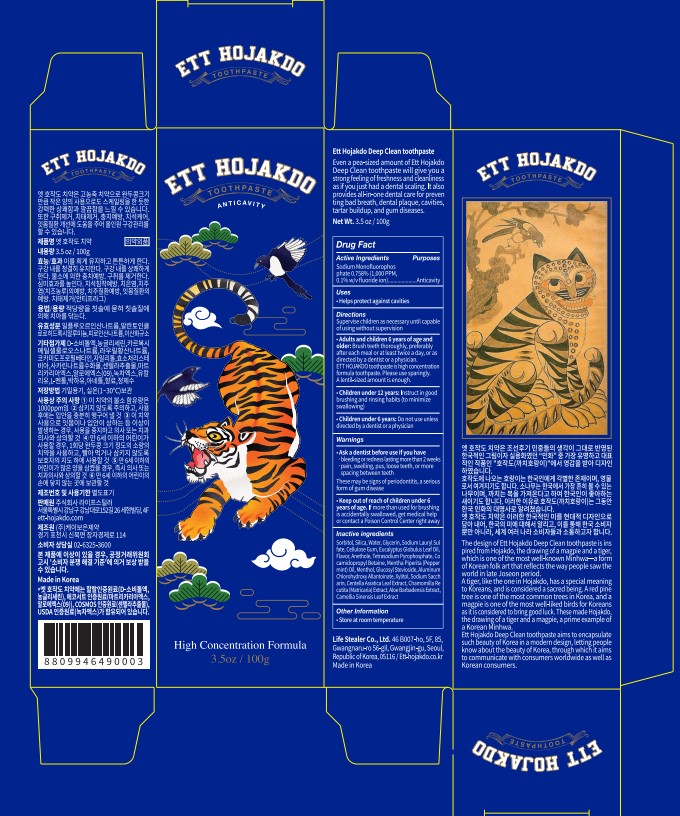 DRUG LABEL: ETT HOJAKDO
NDC: 83672-001 | Form: PASTE, DENTIFRICE
Manufacturer: LIFE STEALER Co., Ltd.
Category: otc | Type: HUMAN OTC DRUG LABEL
Date: 20240116

ACTIVE INGREDIENTS: SODIUM MONOFLUOROPHOSPHATE 0.758 g/100 g
INACTIVE INGREDIENTS: SILICON DIOXIDE; SODIUM PYROPHOSPHATE; ALCLOXA; SORBITOL; GLYCERIN; CARBOXYMETHYLCELLULOSE SODIUM, UNSPECIFIED; SODIUM LAURYL SULFATE; COCAMIDOPROPYL BETAINE; XYLITOL; GLUCOSYL STEVIOL; SACCHARIN SODIUM; CENTELLA ASIATICA LEAF; MATRICARIA CHAMOMILLA WHOLE; ALOE VERA WHOLE; GREEN TEA LEAF; EUCALYPTUS OIL; MENTHOL, UNSPECIFIED FORM; PENNYROYAL OIL; ANETHOLE; WATER

83672-001_ETT HOJAKDO toothpaste

active ingredient

Sodium Monofluorophosphate 0.758%

Keep out of reach of children under 6 years of age.

Purpose

Anticavity

Uses

Helps protect against cavities

Warnings

Ask a dentist before use if you have

- bleeding or redness lasting more than 2 weeks

- pain, waelling, pus, loose teeth, or more spacing between teeth

These may be signs of periodontitis, a serious form of gum disease.

Directions

Adults and children 6 years of age and older

Brush teeth thoroughly, preferably after each meal or at least twice a day, or as directed by a dentist or physician.

ETT HOJAKDO toothpaste is high concentration formula toothpaste. Please use sparingly. A lentil-sized amount is enough.

Children under 12 years old

Instruct in good brushing and rinsing habits (to minimize swallowing)

Children under 6 years old

Do not use unless directed by a dentist or a physician

Inactive Ingredients

Silica, Tetrasodium Pyrophosphate, Alcloxa, Sorbitol, Glycerin, Cellulose Gum, Sodium Lauryl Sulfate, Cocamidopropyl Betaine, Xylitol, Glucosyl stevia, Sodium Saccharin, Centella Asiatica Leaf Extract, Chamomilla Recutita (Matricaria) Extract, Aloe Barbadensis Extract, Camellia Sinensis Leaf Extract, Eucalyptus Globulus Leaf Oil, Menthol, Mentha Pulegium Oil, Anethole, Flavor, Water